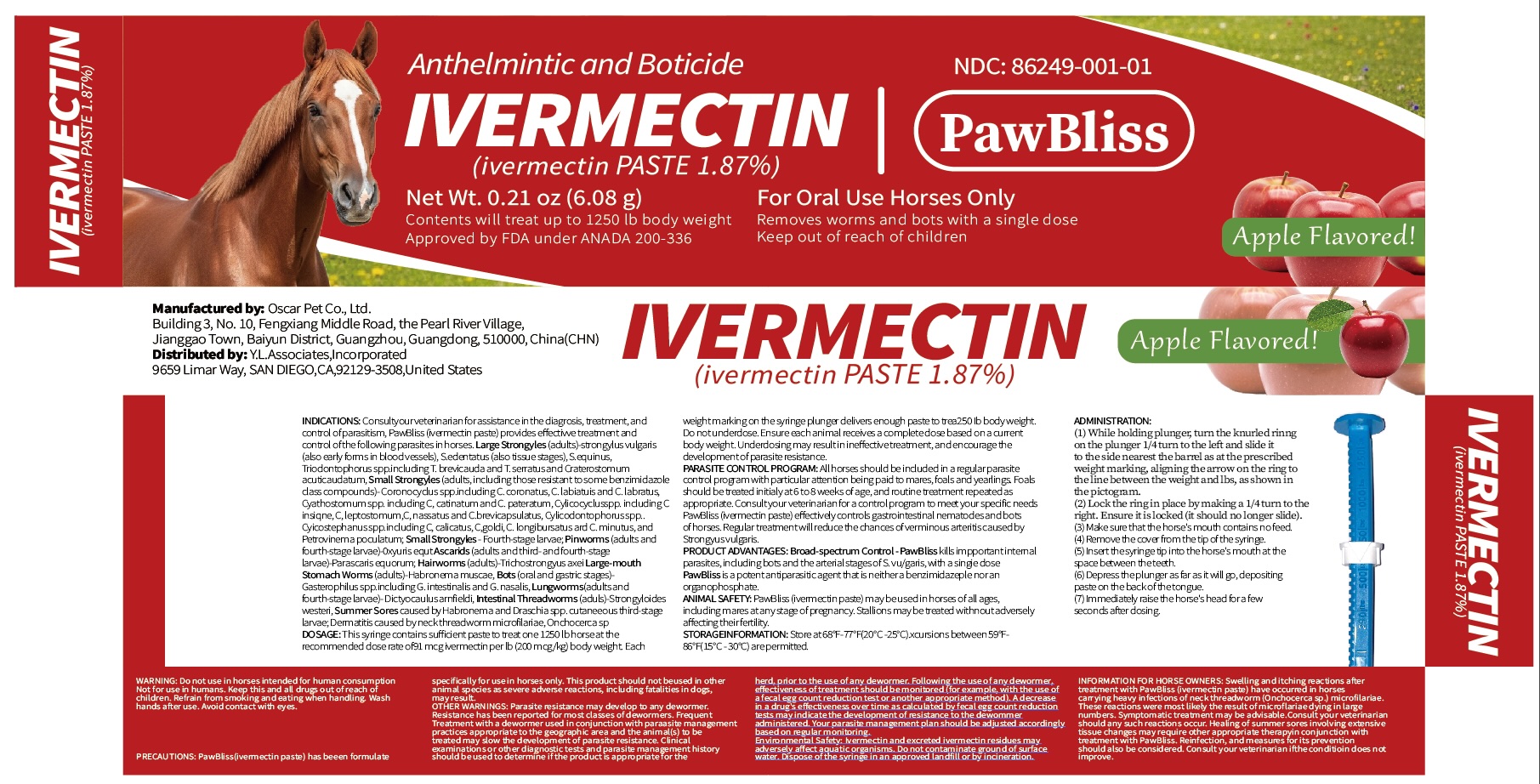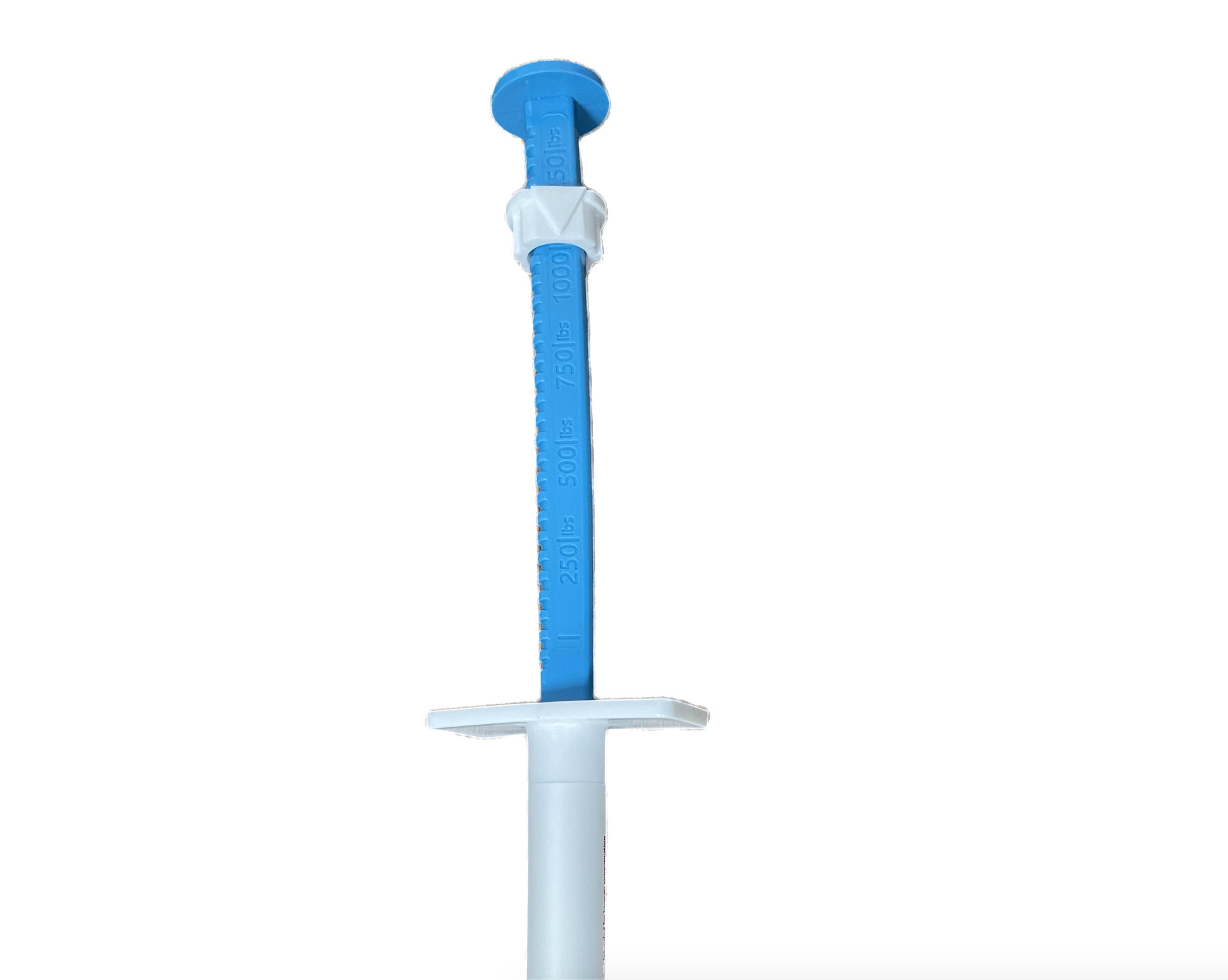 DRUG LABEL: Ivermectin
NDC: 86249-001 | Form: PASTE
Manufacturer: Stellarnet Limited
Category: animal | Type: OTC ANIMAL DRUG LABEL
Date: 20260113

ACTIVE INGREDIENTS: IVERMECTIN 18.7 mg/1 g

PawBliss
Anthelmintic and Boticide
Ivermectin Horse Paste 1.87

DESCRIPTION

For Oral Use in Horses Only

IVERMECTIN
(ivermectin paste) 1.87%

Net Wt. 0.21 oz (6.08 g)

Contents treat up to 1,250 lb body weight

Approved by FDA under ANADA # 200-326

Apple Flavored

Removes worms and bots with a single dose.

INDICATIONS AND USAGE

INDICATIONS: Consult your veterinarian for assistance in the diagnosis, treatment, and control of parasitism. Ivermectin paste provides effective treatment and control of the following parasites in horses: large strongyles (adults), including Strongylus vulgaris (including early forms in blood vessels), S. edentatus (including tissue stages), S. equinus, Triodontophorus spp. including T. brevicauda and T. serratus, and Craterostomum acuticaudatum; small strongyles (adults, including those resistant to some benzimidazole-class compounds), including Coronocyclus spp. (C. coronatus, C. labratus, and C. labiatus), Cyathostomum spp. (C. catinatum and C. pateratum), Cylicocyclus spp. (C. insignis, C. leptostomum, C. nassatus, and C. brevicapsulatus), Cylicodontophorus spp., Cylicostephanus spp. (C. calicatus, C. goldi, C. longibursatus, and C. minutus), and Poteriostomum spp.; small strongyles (fourth-stage larvae); pinworms (adults and fourth-stage larvae), Oxyuris equi; ascarids (adults and third- and fourth-stage larvae), Parascaris equorum; hairworms (adults), Trichostrongylus axei; large-mouthed stomach worms (adults), Habronema muscae; bots (oral and gastric stages), Gasterophilus spp. including G. intestinalis and G. nasalis; lungworms (adults and fourth-stage larvae), Dictyocaulus arnfieldi; intestinal threadworms (adults), Strongyloides westeri; summer sores caused by Habronema and Draschia spp. (cutaneous third-stage larvae); and dermatitis caused by neck threadworm microfilariae (Onchocerca spp.).

DOSAGE AND ADMINISTRATION

DOSAGE: This syringe contains sufficient paste to treat one 1,250 lb horse at the recommended dose rate of 91 mcg ivermectin per lb (200 mcg/kg) of body weight. Each weight marking on the syringe plunger delivers sufficient paste to treat 250 lb of body weight. Do not underdose. Ensure each animal receives a complete dose based on a current body weight. Underdosing may result in ineffective treatment and may encourage the development of parasite resistance.

PARASITE CONTROL PROGRAM: All horses should be included in a regular parasite control program, with particular attention given to mares, foals, and yearlings. Foals should be treated initially at 6 to 8 weeks of age, with routine treatments repeated as appropriate. Consult your veterinarian to develop a parasite control program that meets your specific needs. Ivermectin paste effectively controls gastrointestinal nematodes and bots of horses. Regular treatment reduces the likelihood of verminous arteritis caused by Strongylus vulgaris.

PRODUCT ADVANTAGES: Broad-spectrum control — ivermectin paste eliminates important internal parasites of horses, including bots and the arterial stages of Strongylus vulgaris, with a single dose. Ivermectin is a potent antiparasitic agent that is neither a benzimidazole nor an organophosphate.

WARNINGS

ANIMAL SAFETY: Ivermectin paste may be used in horses of all ages, including mares at any stage of pregnancy. Stallions may be treated without adversely affecting fertility.

STORAGE AND HANDLING

STORAGE INFORMATION: Store at 68°F to 77°F (20°C to 25°C). Excursions between 59°F and 86°F (15°C to 30°C) are permitted.

ADMINISTRATION:

1. While holding the plunger, turn the knurled ring on the plunger one-quarter (1/4) turn to the left and slide it to the position corresponding to the prescribed weight, aligning the arrow on the ring with the line between the weight marking and “lb,” as shown in the pictogram.
2. Lock the ring in place by making a one-quarter (1/4) turn to the right. Ensure that it is locked and no longer slides.
3. Ensure that the horse’s mouth contains no feed.
4. Remove the cover from the tip of the syringe.
5. Insert the syringe tip into the horse’s mouth at the space between the teeth.
6. Depress the plunger as far as it will go, depositing the paste on the back of the tongue.
7. Immediately raise the horse’s head for a few seconds after dosing.

WARNINGS

WARNING: Do not use in horses intended for human consumption. Not for use in humans. Keep this and all drugs out of the reach of children. Refrain from smoking or eating when handling this product. Wash hands after use. Avoid contact with eyes.

PRECAUTIONS

PRECAUTIONS: Ivermectin paste has been formulated specifically for use in horses only. This product should not be used in other animal species, as severe adverse reactions, including fatalities in dogs, may result.

OTHER WARNINGS: Parasite resistance may develop to any dewormer. Resistance has been reported for most classes of dewormers. Frequent treatment with a dewormer, used in conjunction with parasite management practices appropriate to the geographic area and the animal(s) to be treated, may slow the development of parasite resistance. Clinical examinations, diagnostic tests, and parasite management history should be used to determine whether this product is appropriate for the herd prior to the use of any dewormer. Following the use of any dewormer, the effectiveness of treatment should be monitored (for example, through fecal egg count reduction tests or other appropriate methods). A decrease in a drug’s effectiveness over time, as determined by fecal egg count reduction tests, may indicate the development of resistance to the dewormer administered. Parasite management programs should be adjusted accordingly based on regular monitoring.

ENVIRONMENTAL SAFETY: Ivermectin and excreted ivermectin residues may adversely affect aquatic organisms. Do not contaminate ground or surface water. Dispose of the syringe in an approved landfill or by incineration.

INFORMATION FOR HORSE OWNERS: Swelling and itching reactions after treatment with ivermectin paste have occurred in horses carrying heavy infections of neck threadworm (Onchocerca spp.) microfilariae. These reactions are most likely the result of microfilariae dying in large numbers. Symptomatic treatment may be advisable. Consult your veterinarian should any such reactions occur. Healing of summer sores involving extensive tissue changes may require additional appropriate therapy in conjunction with treatment with ivermectin paste. Reinfection and measures for its prevention should also be considered. Consult your veterinarian if the condition does not improve.

Distributed by:

Y.L. Associates, Incorporated

9659 Limar Way
San Diego, CA 92129-3508
United States

PRINCIPAL DISPLAY PANEL - 0.21 oz (6.08 g)

Keep out of the reach of children.

For Oral Use in Horses Only

NDC: 86249-001-01

IVERMECTIN
(ivermectin paste) 1.87%

Net Wt. 0.21 oz (6.08 g)
Contents treat up to 1,250 lb body weight

Approved by FDA under ANADA # 200-326

Apple-Flavored